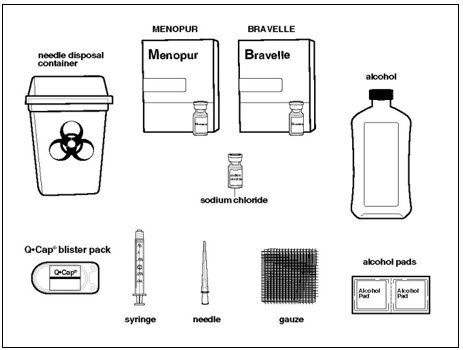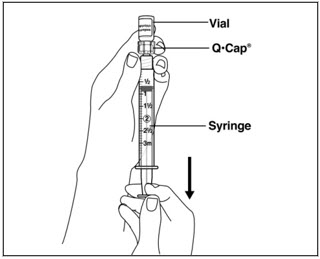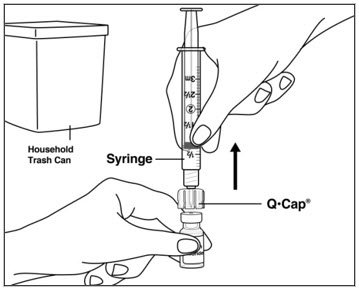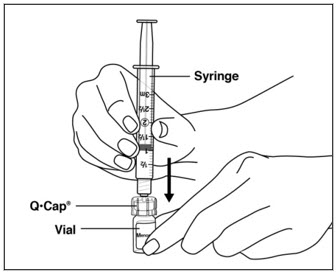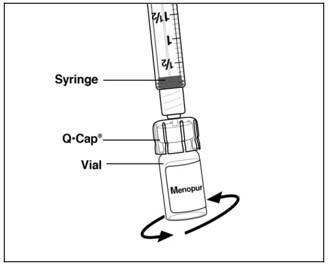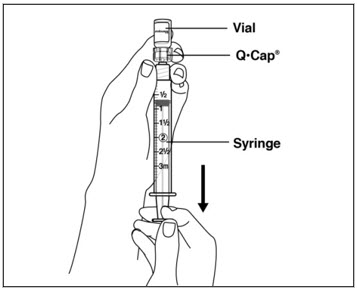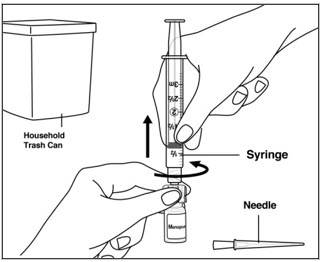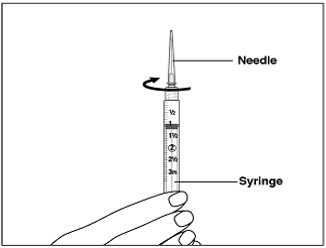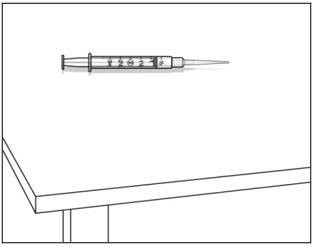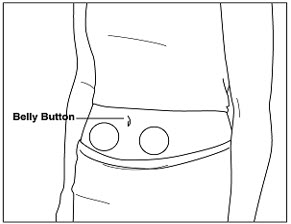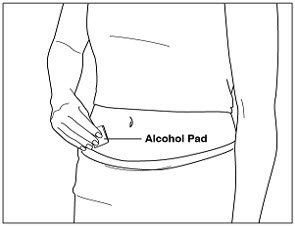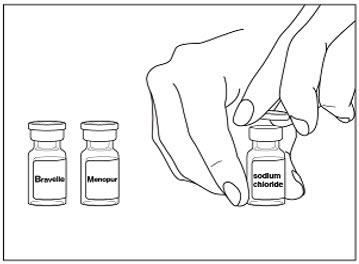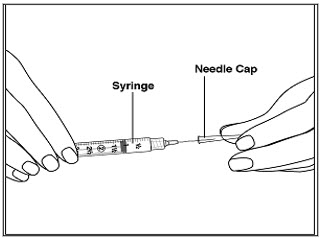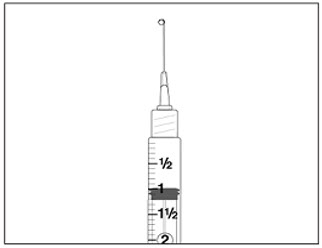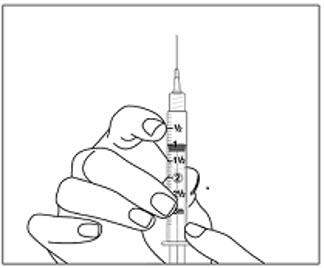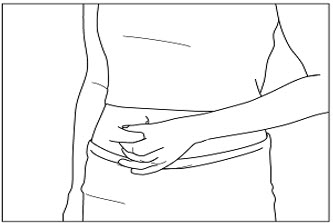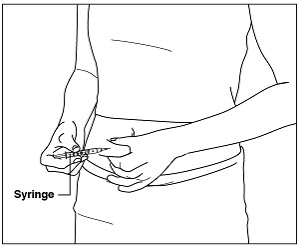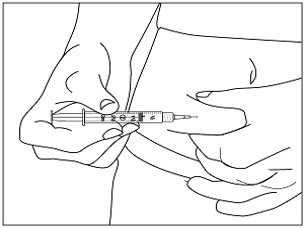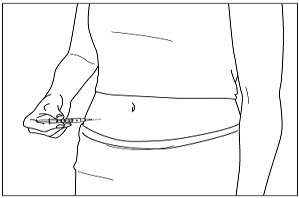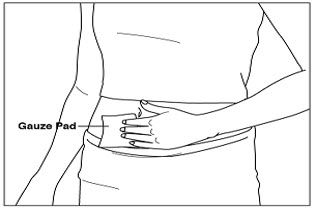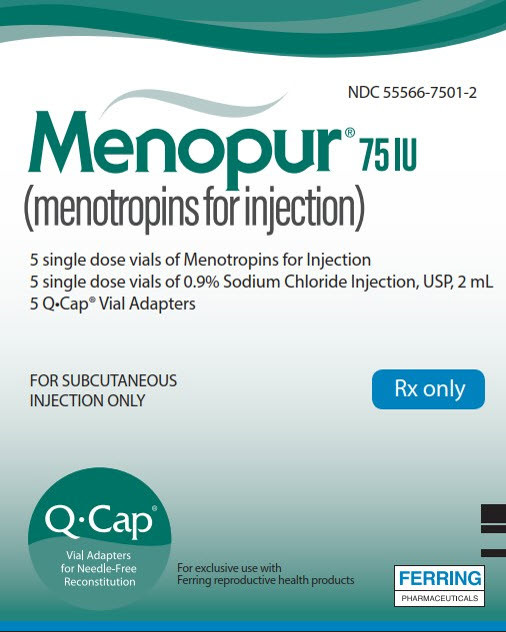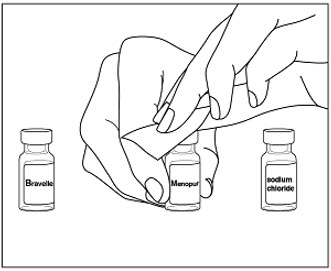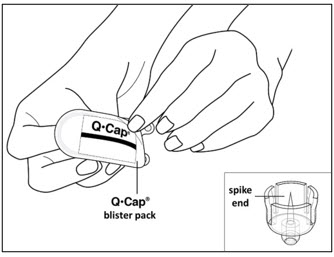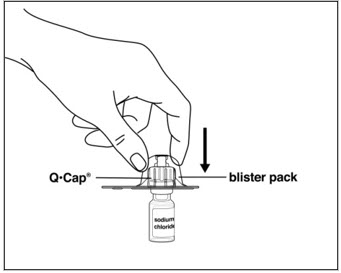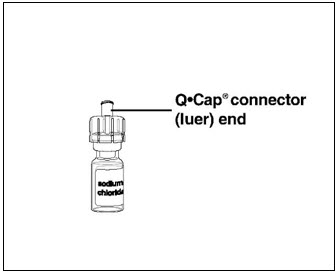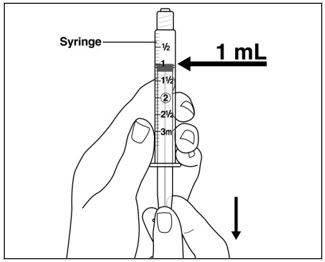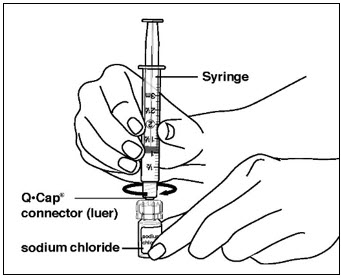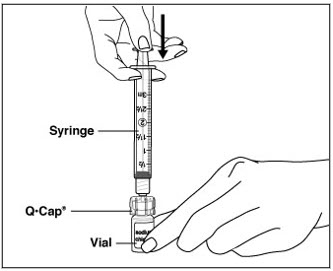 DRUG LABEL: Menopur
NDC: 55566-7501 | Form: KIT | Route: SUBCUTANEOUS
Manufacturer: Ferring Pharmaceuticals Inc.
Category: prescription | Type: HUMAN PRESCRIPTION DRUG LABEL
Date: 20180531

ACTIVE INGREDIENTS: FOLLITROPIN 75 [iU]/1 1; LUTEINIZING HORMONE 75 [iU]/1 1; SODIUM CHLORIDE 9 mg/1 1
INACTIVE INGREDIENTS: LACTOSE MONOHYDRATE 21 mg/1 1; POLYSORBATE 20; SODIUM PHOSPHATE, DIBASIC, HEPTAHYDRATE

HIGHLIGHTS OF PRESCRIBING INFORMATION

These highlights do not include all the information needed to use MENOPUR® safely and effectively. See full prescribing information for MENOPUR.
MENOPUR® (menotropins for injection) for subcutaneous use.
Initial U.S. Approval: 1975

1 INDICATIONS AND USAGE

MENOPUR® (menotropins for injection) is a gonadotropin indicated for:

- Development of multiple follicles and pregnancy in ovulatory women as part of an Assisted Reproductive Technology (ART) cycle (1)

2 DOSAGE AND ADMINISTRATION

- Initial starting dose of the first cycle - 225 International Units per day, administered subcutaneously (2.2)
- Dosage adjustments after 5 days and by no more than 150 International Units at each adjustment (2.2)
- Do not administer doses greater than 450 International Units per day (2.2)
- MENOPUR may be administered together with BRAVELLE® (urofollitropin for injection, purified). Only the total starting dose of 225 International Units (150 International Units of MENOPUR and 75 International Units of BRAVELLE or 75 International Units of MENOPUR and 150 International Units of BRAVELLE) was studied in a clinical trial. (2.2)

3 DOSAGE FORMS AND STRENGTHS

Lyophilized powder for injection: containing 75 IU FSH and 75 IU of LH activity, supplied as lyophilized powder or pellet in sterile vials with diluent vials and Q•Cap® vial adapters. (3)

4 CONTRAINDICATIONS

MENOPUR is contraindicated in women who exhibit:

- Prior hypersensitivity to MENOPUR or menotropins products or one of their excipients (4)
- High levels of FSH indicating primary ovarian failure (4)
- Pregnancy (4)
- Presence of uncontrolled non-gonadal endocrinopathies (4)
- Sex hormone dependent tumors of the reproductive tract and accessory organ (4)
- Tumors of pituitary gland or hypothalamus (4)
- Abnormal uterine bleeding of undetermined origin (4)
- Ovarian cyst or enlargement of undetermined origin, not due to polycystic ovary syndrome (4)

5 WARNINGS AND PRECAUTIONS

- Abnormal Ovarian Enlargement (5.1)
- Ovarian Hyperstimulation Syndrome (OHSS) (5.2)
- Pulmonary and Vascular Complications (5.3)
- Ovarian Torsion (5.4)
- Multi-fetal Gestation and Birth (5.5)
- Congenital Malformation (5.6)
- Ectopic Pregnancy (5.7)
- Spontaneous Abortion (5.8)
- Ovarian Neoplasms (5.9)

6 ADVERSE REACTIONS

The most common adverse reactions (≥2%) in ART include: abdominal cramps; abdomen enlarged; abdominal pain; headache; injection site pain and reaction; injection site inflammation; OHSS (6.1)

To report SUSPECTED ADVERSE REACTIONS, contact Ferring Pharmaceuticals Inc. at 1-888-FERRING (1-888-337-7464) or FDA at 1-800-FDA-1088 or www.fda.gov/medwatch.

7 DRUG INTERACTIONS

No drug/drug interaction studies have been conducted for MENOPUR in humans. (7)

8 USE IN SPECIFIC POPULATIONS

- Pregnancy Category X. Do not use MENOPUR in pregnant women. (4, 8.1)
- Nursing Mothers: It is not known whether this drug is excreted in human milk. (8.3)
- Pediatric Use: Safety and efficacy not established. (8.4)
- Renal and Hepatic Insufficiency: Safety, efficacy, and pharmacokinetics of MENOPUR in women with renal or hepatic insufficiency have not been established. (8.6)

FULL PRESCRIBING INFORMATION

1 INDICATIONS AND USAGE

Development of Multiple Follicles and Pregnancy in Ovulatory Women as Part of an Assisted Reproductive Technology (ART) Cycle

Prior to initiation of treatment with MENOPUR® (menotropins for injection):

- Perform a complete gynecologic and endocrinologic evaluation, and diagnose the cause of infertility
- Exclude the possibility of pregnancy
- Evaluate the fertility status of the male partner
- Exclude a diagnosis of primary ovarian failure

2 DOSAGE AND ADMINISTRATION

2.1 General Dosing Information

- Parenteral drug products should be inspected visually for particulate matter and discoloration prior to administration, whenever solution and container permit.
- Administer MENOPUR subcutaneously in the abdomen as described in Instructions for Use.
- MENOPUR may be administered together with BRAVELLE® (urofollitropin for injection, purified).

2.2 Recommended Dosing for Assisted Reproductive Technology

The recommended dosing scheme for patients undergoing IVF follows a stepwise approach and is individualized for each woman. The recommended initial dose of MENOPUR for women who have received a GnRH agonist for pituitary suppression is 225 International Units. MENOPUR may be administered together with BRAVELLE and the total initial dose when the products are combined should not exceed 225 International Units (150 International Units of MENOPUR and 75 International Units of BRAVELLE or 75 International Units of MENOPUR and 150 International Units of BRAVELLE).

- Beginning on cycle day 2 or 3, a starting dose of 225 International Units of MENOPUR is administered subcutaneously daily. Adjust the dose after 5 days based on the woman's ovarian response, as determined by ultrasound evaluation of follicular growth and serum estradiol levels.
- Do not make additional dosage adjustments more frequently than every 2 days or by more than 150 International Units at each adjustment.
- Continue treatment until adequate follicular development is evident, and then administer hCG. Withhold the administration of hCG in cases where the ovarian monitoring suggests an increased risk of OHSS on the last day of MENOPUR therapy [see Warnings and Precautions (5.1, 5.2, 5.10)].
- Do not administer daily doses of MENOPUR or MENOPUR in combination with BRAVELLE that exceed 450 International Units.
- Therapy should not exceed 20 days.

3 DOSAGE FORMS AND STRENGTHS

Lyophilized powder for Injection containing 75 International Units FSH and 75 International Units of LH activity, supplied as lyophilized powder or pellet in sterile vials with diluent vials and Q•Cap® vial adapters.

4 CONTRAINDICATIONS

MENOPUR is contraindicated in women who exhibit:

- Prior hypersensitivity to MENOPUR or menotropins products or one of their excipients
- High levels of FSH indicating primary ovarian failure [see Indications and Usage (1)]
- Pregnancy
  MENOPUR may cause fetal harm when administered to a pregnant woman [see Use in Specific Populations (8.1)]. MENOPUR is contraindicated in women who are pregnant. If this drug is used during pregnancy, or if the woman becomes pregnant while taking this drug, the woman should be apprised of the potential hazard to a fetus.
- Presence of uncontrolled non-gonadal endocrinopathies (e.g., thyroid, adrenal, or pituitary disorders) [see Indications and Usage (1)]
- Sex hormone dependent tumors of the reproductive tract and accessory organs
- Tumors of pituitary gland or hypothalamus
- Abnormal uterine bleeding of undetermined origin
- Ovarian cyst or enlargement of undetermined origin, not due to polycystic ovary syndrome

5 WARNINGS AND PRECAUTIONS

MENOPUR should only be used by physicians who are experienced in infertility treatment. MENOPUR contains gonadotropic substances capable of causing in women, Ovarian Hyperstimulation Syndrome (OHSS) with or without pulmonary or vascular complications [see Warnings and Precautions (5.2, 5.3)] and multiple births [see Warnings and Precautions (5.5)]. Gonadotropin therapy requires the availability of appropriate monitoring facilities [see Warnings and Precautions (5.10)]. Use the lowest effective dose.

5.1 Abnormal Ovarian Enlargement

In order to minimize the hazards associated with abnormal ovarian enlargement that may occur with MENOPUR therapy, treatment should be individualized and the lowest effective dose should be used [see Dosage and Administration (2.2)]. Use of ultrasound monitoring of ovarian response and/or measurement of serum estradiol levels is important to minimize the risk of ovarian stimulation [see Warnings and Precautions (5.10)].

If the ovaries are abnormally enlarged on the last day of MENOPUR therapy, hCG should not be administered in order to reduce the chance of developing Ovarian Hyperstimulation Syndrome (OHSS) [see Warnings and Precautions (5.2)]. Prohibit intercourse in women with significant ovarian enlargement because of the danger of hemoperitoneum resulting from rupture of ovarian cysts [see Warnings and Precautions (5.2)].

5.2 Ovarian Hyperstimulation Syndrome (OHSS)

OHSS is a medical event distinct from uncomplicated ovarian enlargement and may progress rapidly to become a serious medical event. OHSS is characterized by a dramatic increase in vascular permeability, which can result in a rapid accumulation of fluid in the peritoneal cavity, thorax, and potentially, the pericardium. The early warning signs of development of OHSS are severe pelvic pain, nausea, vomiting, and weight gain. Abdominal pain, abdominal distension, gastrointestinal symptoms including nausea, vomiting and diarrhea, severe ovarian enlargement, weight gain, dyspnea, and oliguria have been reported with OHSS. Clinical evaluation may reveal hypovolemia, hemoconcentration, electrolyte imbalances, ascites, hemoperitoneum, pleural effusion, hydrothorax, acute pulmonary distress, and thromboembolic reactions [see Warnings and Precautions (5.3)]. Transient liver function test abnormalities suggestive of hepatic dysfunction, with or without morphologic changes on liver biopsy, have been reported in association with OHSS.

OHSS occurs after gonadotropin treatment has been discontinued and it can develop rapidly, reaching its maximum about seven to ten days following treatment. Usually, OHSS resolves spontaneously with the onset of menses. If there is evidence that OHSS may be developing prior to hCG administration [see Warnings and Precautions (5.1)], the hCG must be withheld.

Cases of OHSS are more common, more severe, and more protracted if pregnancy occurs; therefore, women should be assessed for the development of OHSS for at least two weeks after hCG administration.

If serious OHSS occurs, gonadotropins, including hCG, should be stopped and consideration should be given as to whether the woman needs to be hospitalized. Treatment is primarily symptomatic and overall should consist of bed rest, fluid and electrolyte management, and analgesics (if needed). Because the use of diuretics can accentuate the diminished intravascular volume, diuretics should be avoided except in the late phase of resolution as described below. The management of OHSS may be divided into three phases as follows:

- Acute Phase:
  Management should be directed at preventing hemoconcentration due to loss of intravascular volume to the third space and minimizing the risk of thromboembolic phenomena and kidney damage. Fluid intake and output, weight, hematocrit, serum and urinary electrolytes, urine specific gravity, BUN and creatinine, total proteins with albumin: globulin ratio, coagulation studies, electrocardiogram to monitor for hyperkalemia, and abdominal girth should be thoroughly assessed daily or more often based on the clinical need. Treatment, consisting of limited intravenous fluids, electrolytes, human serum albumin, is intended to normalize electrolytes while maintaining an acceptable but somewhat reduced intravascular volume. Full correction of the intravascular volume deficit may lead to an unacceptable increase in the amount of third space fluid accumulation.
- Chronic Phase:
  After the acute phase is successfully managed as above, excessive fluid accumulation in the third space should be limited by instituting severe potassium, sodium, and fluid restriction.
- Resolution Phase:
  As third space fluid returns to the intravascular compartment, a fall in hematocrit and increasing urinary output are observed in the absence of any increase in intake. Peripheral and/or pulmonary edema may result if the kidneys are unable to excrete third space fluid as rapidly as it is mobilized. Diuretics may be indicated during the resolution phase, if necessary, to combat pulmonary edema.

Do not remove ascitic, pleural, and pericardial fluid unless there is the necessity to relieve symptoms such as pulmonary distress or cardiac tamponade.

OHSS increases the risk of injury to the ovary. Pelvic examination or intercourse may cause rupture of an ovarian cyst, which may result in hemoperitoneum, and should be avoided.

If bleeding occurs and requires surgical intervention, the clinical objective should be to control the bleeding and retain as much ovarian tissue as possible. A physician experienced in the management of this syndrome, or who is experienced in the management of fluid and electrolyte imbalances, should be consulted.

In the IVF clinical trial for MENOPUR, OHSS occurred in 7.2% of the 373 MENOPUR treated women.

5.3 Pulmonary and Vascular Complications

Serious pulmonary conditions (e.g. atelectasis, acute respiratory distress syndrome, and exacerbation of asthma) have been reported in women treated with gonadotropins. In addition, thromboembolic events both in association with, and separate from the Ovarian Hyperstimulation Syndrome (OHSS) have been reported in women treated with gonadotropins. Intravascular thrombosis and embolism, which may originate in venous or arterial vessels, can result in reduced blood flow to critical organs or the extremities. Women with generally recognized risk factors for thrombosis, such as personal or family history, severe obesity, or thrombophilia, may have an increased risk of venous or arterial thromboembolic events during or following treatment with gonadotropins. Sequelae of such reactions have included venous thrombophlebitis, pulmonary embolism, pulmonary infarction, cerebral vascular occlusion (stroke), and arterial occlusion resulting in loss of limb and rarely in myocardial infarctions. In rare cases, pulmonary complications and/or thromboembolic reactions have resulted in death. In women with recognized risk factors, the benefits of ovulation induction and assisted reproductive technology need to be weighed against the risks. Pregnancy also carries an increased risk of thrombosis.

5.4 Ovarian Torsion

Ovarian torsion has been reported after treatment with gonadotropins. This may be related to OHSS, pregnancy, previous abdominal surgery, past history of ovarian torsion, previous or current ovarian cyst, and polycystic ovaries. Damage to the ovary due to reduced blood supply can be limited by early diagnosis and immediate detorsion.

5.5 Multi-fetal Gestation and Birth

Multi-fetal gestation and births have been reported with all gonadotropin therapy including therapy with MENOPUR.

In the IVF clinical trial of MENOPUR, multiple pregnancy as diagnosed by ultrasound occurred in 35.3% (n=30) of 85 total pregnancies.

Before beginning treatment with MENOPUR, advise the woman and her partner of the potential risk of multi-fetal gestation and birth.

5.6 Congenital Malformations

The incidence of congenital malformations after some ART [specifically in vitro fertilization (IVF) or intracytoplasmic sperm injection (ICSI)] may be slightly higher than after spontaneous conception. This slightly higher incidence is thought to be related to differences in parental characteristics (e.g., maternal age, maternal and paternal genetic background, sperm characteristics) and to the higher incidence of multi-fetal gestations after IVF or ICSI. There are no indications that the use of gonadotropins during IVF or ICSI is associated with an increased risk of congenital malformations.

5.7 Ectopic Pregnancy

Since infertile women undergoing ART often have tubal abnormalities, the incidence of ectopic pregnancy may be increased. Early confirmation of intrauterine pregnancy should be determined by β-hCG testing and transvaginal ultrasound.

5.8 Spontaneous Abortion

The risk of spontaneous abortion (miscarriage) is increased with gonadotropin products. However, causality has not been established. The increased risk may be a factor of the underlying infertility.

5.9 Ovarian Neoplasms

There have been infrequent reports of ovarian neoplasms, both benign and malignant, in women who have had multiple drug therapy for controlled ovarian stimulation; however, a causal relationship has not been established.

5.10 Laboratory Tests

In most instances, treatment of women with MENOPUR will result only in follicular growth and maturation. In the absence of an endogenous LH surge, hCG is given when monitoring of the woman indicates that sufficient follicular development has occurred. This may be estimated by ultrasound alone or in combination with measurement of serum estradiol levels. The combination of both ultrasound and serum estradiol measurement are useful for monitoring follicular growth and maturation, timing of the ovulatory trigger, detecting ovarian enlargement and minimizing the risk of the OHSS and multiple gestation.

The clinical confirmation of ovulation is obtained by direct or indirect indices of progesterone production as well as sonographic evidence of ovulation.

Direct or indirect indices of progesterone production:

- Urinary or serum luteinizing hormone (LH) rise
- A rise in basal body temperature
- Increase in serum progesterone
- Menstruation following the shift in basal body temperature

Sonographic evidence of ovulation:

- Collapsed follicle
- Fluid in the cul-de-sac
- Features consistent with corpus luteum formation
- Secretory endometrium

6 ADVERSE REACTIONS

The following serious adverse reactions are discussed elsewhere in the labeling:

- Abnormal Ovarian Enlargement [see Warnings and Precautions (5.1)]
- Ovarian Hyperstimulation Syndrome [see Warnings and Precautions (5.2)]
- Atelectasis, acute respiratory distress syndrome and exacerbation of asthma [see Warnings and Precautions (5.3)]
- Thromboembolic events [see Warnings and Precautions (5.3)]
- Ovarian Torsion [see Warnings and Precautions (5.4)]
- Multi-fetal Gestation and Birth [see Warnings and Precautions (5.5)]
- Congenital Malformations [see Warnings and Precautions (5.6)]
- Ectopic Pregnancy [see Warnings and Precautions (5.7)]
- Spontaneous Abortion [see Warnings and Precautions (5.8)]
- Ovarian Neoplasms [see Warnings and Precautions (5.9)]

6.1 Clinical Trial Experience

Because clinical trials are conducted under widely varying conditions, adverse reaction rates observed in the clinical trials of a drug cannot be directly compared to rates in the clinical trial of another drug and may not reflect the rates observed in practice.

In two single cycle, open label, multinational, multicenter, comparative trials, a total of 434 normal ovulatory infertile women were randomized and received subcutaneously administered MENOPUR as part of an in vitro fertilization (IVF) cycle (both trials) or intracytoplasmic sperm injection (ICSI) cycle (one of the two trials). All women received pituitary down-regulation with gonadotropin releasing hormone (GnRH) agonist before stimulation. Adverse Reactions occurring at an incidence of ≥ 2% in women receiving MENOPUR are shown in Table 1.

Table 1: MENOPUR Administered Subcutaneously in Women Undergoing IVF and ICSI. Adverse Reactions with Incidence of 2% or Greater Occurring on or After GnRH Administration.
Body System/Preferred Term |  | IVF n=434
Body System/Preferred Term |  | N | %
Body as a whole | Abdominal cramps | 13 | 3.0
Body as a whole | Abdomen enlarged | 10 | 2.3
Body as a whole | Abdominal pain | 29 | 6.7
Body as a whole | Headache | 27 | 6.2
Body as a whole | Injection site pain + reaction | 17 | 3.9
Body as a whole | Injection site inflammation | 10 | 2.3
Urogenital | Ovarian Hyperstimulation Syndrome (OHSS) | 27 | 6.2

In addition, thrombophlebitis was reported in less than 1% of subjects.

In an open label, US, multicenter, comparative IVF and ICSI trial, MENOPUR and BRAVELLE were administered in the same syringe to 60 normal ovulatory infertile women. OHSS, post retrieval cramping and nausea and spontaneous abortion were the most common adverse reactions occurring at an incidence of ≥ 5% in women receiving the combination of MENOPUR and BRAVELLE.

In another open label, US multicenter, comparative trial for ovulation induction in anovulatory or oligovulatory infertile women, 76 subjects received subcutaneous or intramuscular injections of MENOPUR. The most common adverse reactions occurring at an incidence of ≥ 5% in women receiving MENOPUR were: headache; OHSS; injection site reaction, abdominal cramps, fullness and pain; and nausea.

6.2 Postmarketing Experience

The following adverse reactions have been reported during postmarketing use of gonadotropins. Because these reactions were reported voluntarily from a population of uncertain size, the frequency or a causal relationship to MENOPUR cannot be reliably determined.

Gastrointestinal disorders: abdominal pain, abdominal pain lower, abdominal distension, nausea, vomiting, abdominal discomfort

General disorders and administration site conditions: injection site reactions (most frequently reported injection site reaction was injection site pain), fatigue

Nervous system disorders: headache, dizziness

Reproductive system disorders: OHSS [see Warnings and Precautions (5.2)], pelvic pain, ovarian cyst, breast complaints (including breast pain, breast tenderness, breast discomfort, and breast swelling)

Skin and subcutaneous tissue disorders: acne, rash

Vascular disorders: hot flush

7 DRUG INTERACTIONS

No drug/drug interaction studies in humans have been conducted for MENOPUR.

8 USE IN SPECIFIC POPULATIONS

8.1 Pregnancy

Teratogenic effects

Pregnancy Category X [see Contraindications (4)].

8.3 Nursing Mothers

It is not known whether this drug is excreted in human milk. Because many drugs are excreted in human milk and because of the potential for serious adverse reactions in the nursing infant from MENOPUR, a decision should be made whether to discontinue nursing or to discontinue the drug, taking into account the importance of the drug to the mother.

8.4 Pediatric Use

Safety and effectiveness in pediatric patients have not been established.

8.6 Renal and Hepatic Insufficiency

Safety, efficacy, and pharmacokinetics of MENOPUR in women with renal or hepatic insufficiency have not been established.

10 OVERDOSAGE

Aside from possible OHSS [see Warnings and Precautions (5.2)] and multiple gestations [see Warnings and Precautions (5.5)], there is no additional information on the consequences of acute overdosage with MENOPUR.

11 DESCRIPTION

MENOPUR is a preparation of gonadotropins (FSH and LH activity), extracted from the urine of postmenopausal women, which has undergone additional steps for purification.

MENOPUR is a sterile, lyophilized powder intended for subcutaneous (SC) injection after reconstitution with sterile 0.9% Sodium Chloride Injection, USP. Each vial of MENOPUR contains 75 International Units of follicle-stimulating hormone (FSH) activity and 75 International Units of luteinizing hormone (LH) activity, plus 21 mg lactose monohydrate and 0.005 mg Polysorbate 20 and Sodium Phosphate Buffer (Sodium Phosphate Dibasic, Heptahydrate and Phosphoric Acid).

The biological activity of MENOPUR is determined using the bioassays for FSH (ovarian weight gain assay in female rats) and LH (seminal vesicle weight gain assay in male rats), modified to increase the accuracy and reproducibility of these assays. The FSH and LH activity assays are standardized using the Fourth International Standard for Urinary FSH and Urinary LH, November 2000, by the Expert Committee on Biological Standardization of the World Health Organization (WHO ECBS). Both FSH and LH are glycoproteins that are acidic and water-soluble. Human Chorionic Gonadotropin (hCG) is detected in MENOPUR.

MENOPUR has been mixed in vitro with BRAVELLE with no evidence of aggregation.

Therapeutic class: Infertility

12 CLINICAL PHARMACOLOGY

12.1 Mechanism of Action

MENOPUR, administered for 7 to 20 days, produces ovarian follicular growth and maturation in women who do not have primary ovarian failure. Treatment with MENOPUR in most instances results only in follicular growth and maturation. When sufficient follicular maturation has occurred, hCG must be given to induce ovulation.

12.3 Pharmacokinetics

Two open-label, randomized, controlled trials were conducted to assess the pharmacokinetics of MENOPUR. Study 2003-02 compared single doses of subcutaneous administration of the US and European (EU) formulations of MENOPUR in 57 healthy, pre-menopausal females who had undergone pituitary suppression. The study established that the two formulations are bioequivalent. Study 2000-03 assessed single and multiple doses of MENOPUR administered subcutaneously and intramuscularly in a 3 phase crossover design in 33 healthy, pre-menopausal females who had undergone pituitary suppression. The primary pharmacokinetic endpoints were FSH AUC and Cmax values. The results are summarized in Table 2.

Table 2: FSH Pharmacokinetic Parameters [Mean (SD)] Following MENOPUR Administration (Study 2000-03)
PK Parameters | Single Dose (225 IU) |  | Multiple Dose (225 IU × 1 day then 150 IU × 6 days)
PK Parameters | Subcutaneous | Intramuscular | Subcutaneous | Intramuscular
Cmax [Single dose Cmax, AUC120 and multiple dose Cmaxss, AUCss] (mIU/mL) | 8.5 (2.5) | 7.8 (2.4) | 15.0 (3.6) | 12.5 (2.3)
Tmax (hr) | 17.9 (5.8) | 27.5 (25.4) | 8.0 (3.0) | 9.0 (7.0)
AUC† (hr-mlU/mL) | 726.2 (243.0) | 656.1 (233.7) | 622.7 (153.0) | 546.2 (91.2)

Absorption

The subcutaneous route of administration trends toward greater bioavailability than the intramuscular route for single and multiple doses of MENOPUR.

Distribution

Human tissue or organ distribution of FSH and LH has not been studied for MENOPUR.

Metabolism

Metabolism of FSH and LH has not been studied for MENOPUR in humans.

Excretion

The elimination half-lives for FSH in the multiple-dose phase were similar (11-13 hours) for subcutaneously administered MENOPUR and intramuscularly administered MENOPUR.

13 NONCLINICAL TOXICOLOGY

13.1 Carcinogenesis, Mutagenesis, Impairment of Fertility

Long-term toxicity studies in animals have not been performed to evaluate the carcinogenic potential of menotropins.

14 CLINICAL STUDIES

The efficacy of MENOPUR was established in one randomized, open-label, multicenter, multinational (in Europe and Israel), comparative clinical trial of women undergoing in vitro fertilization (IVF) or IVF plus intracytoplasmic injection (ICSI) to achieve pregnancy.

All women began ovarian stimulation as part of an IVF cycle following pituitary suppression with a GnRH agonist. A total of 373 patients were randomized to the MENOPUR arm. Randomization was stratified by insemination technique [conventional IVF vs. ICSI]. Efficacy was assessed based on the primary efficacy parameter of continuing pregnancy. The initial daily dose of MENOPUR was 225 International Units administered subcutaneously for five days. Thereafter, the dose was individualized according to each patient's response, up to a maximum of 450 IU/day for a total maximum duration of stimulation of 20 days. Treatment outcomes are summarized in Table 3.

Table 3: Efficacy Outcome in IVF Study (one cycle of treatment)
Parameter | Subcutaneously Administered MENOPUR
 | n=373
Continuing Pregnancy (%) [Continuing pregnancy was defined as ultrasound visualization of gestational sac with fetal heartbeat at ≥10 weeks after ET] | 87 (23) [Non-inferior to comparator recombinant human FSH based on a two-sided 95% confidence interval, intent-to-treat analysis]
Clinical Pregnancy (%) | 98 (26) [Secondary efficacy parameter. Study was not powered to demonstrate differences in this parameter]

16 HOW SUPPLIED/STORAGE AND HANDLING

16.1 How Supplied

MENOPUR (menotropins for injection) is supplied in sterile vials as a lyophilized, white to off-white powder or pellet.

Each vial of MENOPUR is accompanied by a vial of sterile diluent containing 2 mL of 0.9% Sodium Chloride for Injection, USP:

75 International Units FSH and 75 International Units of LH activity, supplied as

NDC 55566-7501-2: Box of 5 vials + 5 vials diluent + 5 Q•Cap vial adapters

16.2 Storage and Handling

Lyophilized powder may be stored refrigerated or at room temperature (3° to 25° C/37° to 77°F) until dispensed. Protect from light. Use immediately after reconstitution. Discard unused material.

17 PATIENT COUNSELING INFORMATION

See FDA-approved patient labeling (Patient Information and Instructions for Use).

17.1 Dosing and Use

Instruct women on the correct usage and dosing of MENOPUR [see Dosage and Administration (2.2)]. Caution women not to change the dosage or the schedule of administration unless she is told to do so by her healthcare provider.

17.2 Duration and Monitoring Required

Prior to beginning therapy with MENOPUR, inform women about the time commitment and monitoring procedures necessary for treatment [see Dosage and Administration (2.2) and Warnings and Precautions (5.10)].

17.3 Instructions Regarding a Missed Dose

Inform the woman that if she misses or forgets to take a dose of MENOPUR, the next dose should not be doubled and she should call her healthcare provider for further dosing instructions.

17.4 Ovarian Hyperstimulation Syndrome

Inform women regarding the risks of OHSS [see Warnings and Precautions (5.2)] and OHSS-associated symptoms including lung and blood vessel problems [see Warnings and Precautions (5.3)] and ovarian torsion [see Warnings and Precautions (5.4)] with the use of MENOPUR.

17.5 Multi-fetal Gestation and Birth

Inform women regarding the risk of multi-fetal gestation and birth with the use of MENOPUR [see Warnings and Precautions (5.5)]

Vials of sterile diluent of 0.9% Sodium Chloride Injection, USP manufactured for Ferring Pharmaceuticals Inc.

MANUFACTURED FOR:
FERRING PHARMACEUTICALS INC.
PARSIPPANY, NJ 07054

8109000033
Rev: 05/2018

Patient Information

MENOPUR® (Men-oh-pyoor)
(menotropins for injection)
for subcutaneous use

Read this Patient Information before you start using MENOPUR® (menotropins for injection) and each time you get a refill. There may be new information. This information does not take the place of talking to your healthcare provider about your medical condition or your treatment.

What is MENOPUR?

MENOPUR is a prescription medicine that contains follicle stimulating hormone (FSH) and luteinizing hormone (LH). MENOPUR causes your ovaries to make multiple (more than 1) eggs as part of an Assisted Reproductive Technology (ART) cycle.

Who should not use MENOPUR?

Do not use MENOPUR if you:

- are allergic to menotropins or any of the ingredients in MENOPUR. See the end of this leaflet for a complete list of ingredients in MENOPUR.
- have ovaries that no longer make eggs (primary ovarian failure)
- are pregnant or think you may be pregnant. If MENOPUR is taken while you are pregnant, it may harm your baby.
- have problems with your thyroid gland, adrenal gland or pituitary gland that are not controlled by taking medicine.
- have a tumor in your female organs, including your ovaries, breast, or uterus that may get worse with high levels of estrogen
- have a tumor of your pituitary gland or hypothalamus
- have abnormal bleeding from your uterus or vagina and the cause is not known
- have ovarian cysts or enlarged ovaries, not due to a problem called polycystic ovary syndrome (PCOS)

What should I tell my healthcare provider before using MENOPUR?

Before you use MENOPUR, tell your healthcare provider if you:

- have been told by a healthcare provider that you are at an increased risk for blood clots (thrombosis)
- have ever had a blood clot (thrombosis), or anyone in your family has ever had a blood clot
- had twisting of your ovary (ovarian torsion)
- had or have a cyst in your ovary
- have any other medical conditions
- are breast feeding or plan to breast feed. It is not known if MENOPUR passes into your breast milk. You and your healthcare provider should decide if you will use MENOPUR or breastfeed. You should not do both.

Tell your healthcare provider about all the medicines you take, including prescription and over-the-counter medicines, vitamins, and herbal supplements.

Know the medicines you take. Keep a list of them to show your healthcare provider and pharmacist when you get a new medicine.

How should I use MENOPUR?

- Read the Instructions for Use at the end of this Patient Information about the right way to use MENOPUR or MENOPUR mixed with BRAVELLE® (urofollitropin for injection, purified).
- Use MENOPUR exactly as your healthcare provider tells you to use it.
- Your healthcare provider will tell you how much MENOPUR to use and when to use it.
- Your healthcare provider may change your dose of MENOPUR if needed.
- If you miss a dose of MENOPUR, call your healthcare provider right away. Do not double the amount of MENOPUR you are using.
- You may need more than 1 vial of MENOPUR for your dose.
- MENOPUR may be mixed with BRAVELLE in the same syringe.

What are possible side effects of MENOPUR?

MENOPUR may cause serious side effects, including:

- ovaries that are too large. MENOPUR may cause your ovaries to be abnormally large. Symptoms of large ovaries include bloating or pain in your lower stomach (pelvic) area. If your ovaries become too large your healthcare provider may tell you that you should not have intercourse (sex) so you do not rupture an ovarian cyst.
- ovarian hyperstimulation syndrome (OHSS). Using MENOPUR may cause OHSS. OHSS is a serious medical condition that can happen when your ovaries produce too many eggs (overstimulated). OHSS can cause fluid to suddenly build up in the area of your stomach, chest, heart, and cause blood clots to form. OHSS may also happen after you stop using MENOPUR. Stop using MENOPUR and call your healthcare provider or go to the nearest hospital emergency room right away if you have any of the following symptoms of OHSS:

- severe pelvic or stomach pain
- nausea
- vomiting
- sudden weight gain

- swollen stomach
- diarrhea
- trouble breathing
- decreased or no urine

- lung problems. MENOPUR may cause serious lung problems that can sometimes lead to death including fluid in the lungs, trouble breathing, and worsening of asthma.
- blood clots. MENOPUR may increase your chance of having blood clots in your blood vessels. Blood clots can cause:
  - blood vessel problems (thrombophlebitis)
  - stroke
  - loss of your arm or leg
  - blood clot in your lung (pulmonary embolus)
- twisting (torsion) of your ovary. MENOPUR may increase the chance of your ovary twisting, if you already have certain conditions such as OHSS, pregnancy, and previous abdominal surgery. Twisting of your ovary may lead to blood flow being cut off to your ovary.
- pregnancy with and birth of multiple babies. MENOPUR may increase your chance of having a pregnancy with more than 1 baby. Having a pregnancy and giving birth to more than 1 baby at a time increases the health risk for you and your babies. Your healthcare provider should talk to you about your chances of multiple births before you start using MENOPUR.
- birth defects. Babies born after ART may have an increased chance of birth defects. Your age, certain sperm problems, your genetic background, and that of your partner, and a pregnancy with more than 1 baby at a time may increase the chance that your baby may have birth defects.
- ectopic pregnancy (pregnancy outside your womb). MENOPUR may increase your chance of having a pregnancy that is abnormally outside of your womb. Your chance of having a pregnancy outside of your womb is increased if you also have fallopian tube problems.
- miscarriage. Your chance of loss of an early pregnancy may be increased if you had difficulty becoming pregnant.
- tumors of the ovary. If you have used medicines like MENOPUR more than 1 time to get pregnant, you may have an increased chance of having tumors in your ovaries, including cancer.

The most common side effects of MENOPUR include:

- stomach cramps, fullness or pain
- headache
- injection site swelling, heat, redness and pain

These are not all the possible side effects of MENOPUR. For more information, ask your healthcare provider or pharmacist.

Tell your healthcare provider if you have any side effect that bothers you or that does not go away.

How should I store MENOPUR?

- Before mixing, store MENOPUR powder in the refrigerator or at room temperature between 37°F to 77°F (3°C to 25°C).
- Protect MENOPUR from light.
- MENOPUR should be used right after mixing.
- Throw away any unused MENOPUR.

Keep MENOPUR and all medicines out of the reach of children.

General Information about the safe and effective use of MENOPUR.

Medicines are sometimes prescribed for purposes other than those listed in a Patient Information leaflet. Do not use MENOPUR for a condition for which it was not prescribed. Do not give MENOPUR to other people, even if they have the same condition you have. It may harm them.

This Patient Information summarizes the most important information about MENOPUR. If you would like more information, talk with your healthcare provider. You can ask your healthcare provider or pharmacist for information about MENOPUR that is written for health professionals.

For more information go to www.menopur.com, or call 1-888-FERRING (1-888-337-7464).

What are the ingredients in MENOPUR?

Active ingredient: menotropins
Inactive ingredients: lactose monohydrate, polysorbate, sodium phosphate buffer (sodium phosphate dibasic, heptahydrate and phosphoric acid)

Instructions for Use

MENOPUR® (Men-oh-pyoor)
(menotropins for injection)
for subcutaneous use

Your healthcare provider should show you how to mix and inject MENOPUR® (menotropins for injection) or MENOPUR mixed with BRAVELLE® (urofollitropin for injection, purified) before you do it for the first time. Before using MENOPUR or MENOPUR mixed with BRAVELLE for the first time, read this Instructions for Use carefully. Keep this leaflet in a safe place and read it when you have questions.

Supplies you will need to give your injection of MENOPUR or MENOPUR mixed with BRAVELLE. See Figure A.

- a clean, flat surface to work on, like a table
- vials of MENOPUR powder (and BRAVELLE powder if you are going to mix the 2 medicines)
- 1 vial of 0.9% Sodium Chloride, USP used for mixing the medicine
- alcohol pads
- rubbing alcohol
- gauze pads
- 1 sterile syringe and 1 sterile needle with cap. Your healthcare provider should tell you which syringe and needle to use.
- the Q•Cap® (vial adapter) that comes with your medicine
- a sharps disposal container for throwing away your used needles and syringes. See "Disposing of your used needles and syringes" at the end of these instructions.

Step 1. Preparing your MENOPUR or MENOPUR mixed with BRAVELLE.

- Wash your hands well with soap and water and dry them with a clean towel.
- Place all the supplies you need on the clean surface you already prepared.
- Check the vial(s) of MENOPUR (and BRAVELLE if needed) to make sure there is powder or a pellet in the vial(s). If you do not see any powder in the vial(s) do not use the vial and call your pharmacist or healthcare provider.
- Check the 0.9% Sodium Chloride, USP vial to make sure that the liquid is clear and does not contain any particles. If you see any particles in the liquid or the liquid is discolored, do not use the vial and call your pharmacist or healthcare provider.
- Check the Q•Cap blister pack package to make sure it is intact. Do not use if the package is damaged.
- Remove the plastic cap(s) from the vial(s) of MENOPUR (and BRAVELLE if needed) and 0.9% Sodium Chloride, USP vial(s). See Figure B.
- Wipe the tops of the vials with alcohol and allow them to dry. Do not touch the tops of the vials after you have wiped them. See Figure C.
- Place the vial of 0.9% Sodium Chloride, USP on the table.
- Open the Q•Cap blister pack by peeling back the lidding (See Figure D). Do not take the Q•Cap out of the blister pack at this time. Do not touch the spike or connector (luer) ends of the Q•Cap.
- Hold the 0.9% Sodium Chloride, USP vial in 1 hand. With your other hand, hold the sides of the Q•Cap blister pack, turn the Q•Cap blister pack over, and place it on top of the vial. Push the Q•Cap straight down into the rubber stopper of the vial until the Q•Cap spike pierces the top of the vial and snaps into place. See Figure E.
  - Do not use the Q•Cap if it falls out of the blister pack. Throw it away and get a new one.
- Remove the blister pack and throw it away in your household trash. Do not touch the connector end (luer) of the Q•Cap. See Figure F.
- Take the syringe and pull down on the syringe plunger rod until you have reached the line that corresponds with the amount of 0.9% Sodium Chloride, USP that your healthcare provider told you to use (typically 1 mL). Air is just being drawn into the syringe at this step. See Figure G.
  NOTE: The usual amount of 0.9% Sodium Chloride, USP used to mix your MENOPUR is 1 mL.
  - Be very careful not to touch the syringe plunger during this step.
- Place the tip of the syringe into the connector end (luer) of the Q•Cap then twist the syringe clockwise until it is tight. Be careful not to overtighten the syringe. See Figure H.
- Slowly push down on the syringe plunger to push the air from the syringe into the vial. See Figure I.
- Keeping the syringe and Q•Cap together, turn the vial upside down and pull down on the syringe plunger to withdraw the right amount of 0.9% Sodium Chloride, USP from the vial. Your healthcare provider should tell you the right amount of 0.9% Sodium Chloride, USP to use. See Figure J.
- Separate the Q•Cap and syringe from the vial by pulling up on the syringe barrel. Do not pull the plunger to remove the Q•Cap. Throw away 0.9% Sodium Chloride, USP vial in your household trash. See Figure K.
- Hold the vial of MENOPUR powder in 1 hand. With your other hand, hold the sides of the syringe with the Q•Cap attached and place the tip of the Q•Cap over the top of the vial. Push the tip of the Q•Cap into the rubber stopper on the top of the vial until it stops and snaps into place. Be careful not to push down on the syringe plunger during this step. See Figure L. You may see the powder dissolve as the Q•Cap snaps into place, but continue with the steps listed below.
- Slowly push down on the syringe plunger to push the 0.9% Sodium Chloride, USP into the vial with the MENOPUR powder in it. The entire amount of the 0.9% Sodium Chloride, USP in the syringe should be added. Gently swirl the vial until the MENOPUR powder is completely dissolved. Do not shake the vial as this will cause bubbles. See Figure M.
- As soon as the powdered medicine has completely dissolved, push the plunger down to empty any remaining air from the syringe, then turn the vial upside down and slowly pull down on the plunger to withdraw all of the MENOPUR into the syringe. See Figure N.
  - Be careful not to pull the plunger stopper all the way out of the syringe barrel.

If your healthcare provider tells you to use more than 1 vial of MENOPUR or tells you to mix your MENOPUR with BRAVELLE in the same syringe:

- Mix your first vial of MENOPUR powder or BRAVELLE powder with 0.9% Sodium Chloride, USP. Do not inject your dose yet.
- Use the liquid in the syringe you have just mixed to mix the next vial of MENOPUR or BRAVELLE. See Figures K through M.
- You can use the liquid in the syringe to mix up to 5 more vials of medicine.
- Your healthcare provider will tell you how many vials of MENOPUR and BRAVELLE to use.

Step 2. Removing the Q•Cap and adding your needle for injection.

- When you have finished mixing the last vial needed for your injection and have withdrawn all the medicine into the syringe, remove the syringe from the Q•Cap by twisting the syringe counter-clockwise while holding the Q•Cap steady. See Figure O. Throw away the Q•Cap with the attached vial into your household trash.
- You are now ready to attach the needle to the syringe for your injection.
  Your healthcare provider will tell you what needle you should use for your injection.
- While holding the syringe with the syringe tip pointing up, place the needle on the top of the syringe. Gently push down on the needle and twist the needle onto the syringe in a clockwise direction until it is tight. See Figure P.
- Do not remove the needle cap until you are ready for your injection.(See Step 4)
  - Carefully set the syringe with the needle down on the table. See Figure Q.

Step 3. Prepare Injection site for MENOPUR or MENOPUR mixed with BRAVELLE.

- Select a site to inject MENOPUR or MENOPUR mixed with BRAVELLE on your stomach area (abdomen).
  - Pick a site on your lower abdomen, 1-2 inches below the navel, alternating between left and right sides.
  - Each day, inject in a different site to help reduce soreness and skin problems. For example, on day 1, inject yourself on the right side of your abdomen. The next day, inject yourself on the left side of your abdomen. Changing your injection sites every day will help reduce soreness and skin problems. See Figure R.
- Clean your injection site with an alcohol pad. Let the alcohol dry. See Figure S.
- Carefully remove the needle cap from the syringe. See Figure T.
- Hold the syringe with the needle pointing straight up. Pull down slightly on the plunger and tap the barrel of the syringe so that any air bubbles rise to the top. Slowly press the plunger up until all the air is out of the syringe and a small drop of liquid is seen at the tip of the needle. See Figure U.
- Tap the syringe to remove the small drop of liquid at the tip of the needle. Do not let the needle touch anything to keep it sterile. See Figure V.
- The medicine is now ready for you to inject. See Figure V.

Step 4: Injection

- Hold the syringe in 1 hand. Use your other hand to gently pinch a fold of cleaned skin where you will insert your needle. Hold the skin between your thumb and index finger. See Figure W.
- Hold your syringe at a right angle to your skin. Quickly insert the needle all the way into your skin fold. See Figure X.
- Push down the plunger of the syringe with a steady motion. Keep pushing until all the fluid is injected into your skin. See Figure Y.
- Let go of your skin fold and pull the needle straight out of your skin. See Figure Z.

Step 5. After your injection.

- If there is any bleeding at your injection site, place a gauze pad over your injection site. Apply gentle pressure to stop the bleeding. Do not rub the site. See Figure AA.
- If your injection site becomes sore or red, you may put ice on your injection site for 1 minute and then take it off for 3 minutes. If needed, you may repeat this 3 or 4 times.

Step 6. Disposing of your used needles and syringes.

- Put your used needles and syringes in a FDA-cleared sharps disposal container right away after use. Do not throw away loose needles and syringes in your household trash.
- If you do not have a FDA-cleared sharps disposal container, you may use a household container that:
  - is made of a heavy-duty plastic,
  - can be closed with a tight-fitting, puncture-resistant lid, without sharps being able to come out,
  - remains upright and stable during use,
  - is leak-resistant, and
  - is properly labeled to warn of hazardous waste inside the container.
- When your sharps disposal container is almost full, you will need to follow your community guidelines for the right way to dispose of your sharps disposal container. There may be state or local laws about how you should throw away used needles and syringes. For more information about safe sharps disposal, and for specific information about sharps disposal in the state that you live in, go to the FDA's website at: http://www.fda.gov/safesharpsdisposal.

Do not dispose of your used sharps disposal container in your household trash unless your community guidelines permit this. Do not recycle your used sharps disposal container.

This Instructions for Use has been approved by the U.S. Food and Drug Administration.

MANUFACTURED FOR:
FERRING PHARMACEUTICALS INC.
PARSIPPANY, NJ 07054

8109000033
Rev: 05/2018

PRINCIPAL DISPLAY PANEL - Kit Carton

NDC 55566-7501-2

Menopur® 75 IU
(menotropins for injection)

5 single dose vials of Menotropins for Injection
5 single dose vials of 0.9% Sodium Chloride Injection, USP, 2 mL
5 Q•Cap® Vial Adapters

FOR SUBCUTANEOUS
INJECTION ONLY

Rx only

Q•Cap®
Vial Adapters
for Needle-Free
Reconstitution

For exclusive use with
Ferring reproductive health products

FERRING
PHARMACEUTICALS